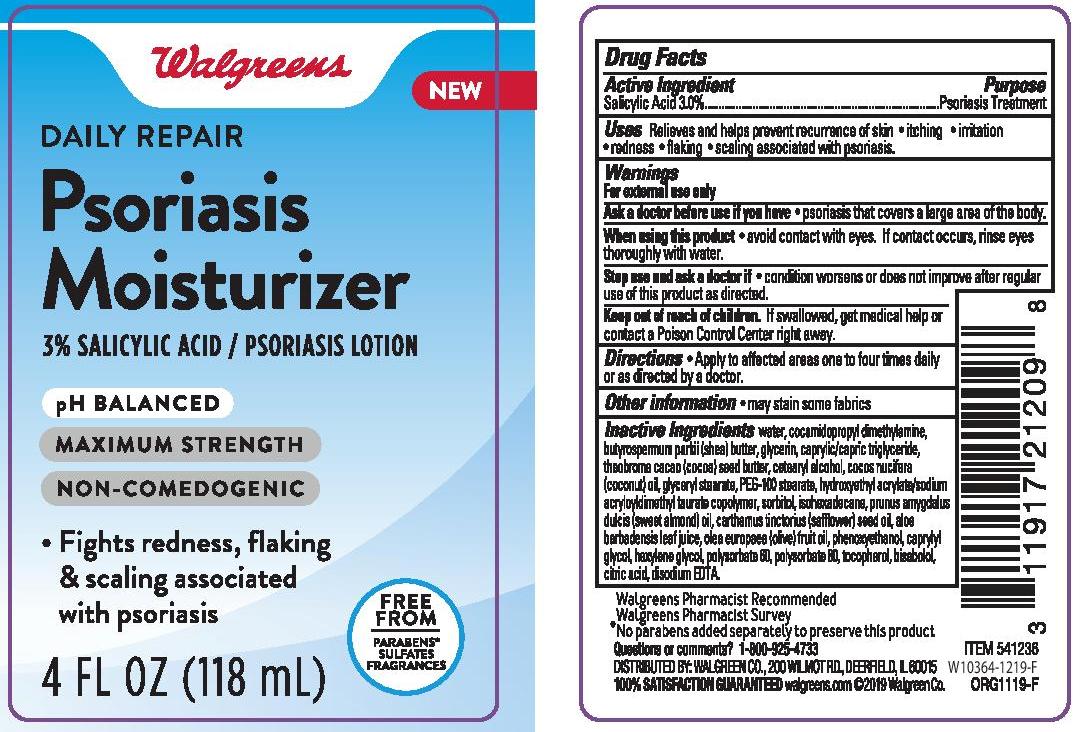 DRUG LABEL: WALGREENS DAILY REPAIR PSORIASIS MOISTURIZER
NDC: 0363-0920 | Form: LOTION
Manufacturer: WALGREEN COMPANY
Category: otc | Type: HUMAN OTC DRUG LABEL
Date: 20241014

ACTIVE INGREDIENTS: SALICYLIC ACID 30 mg/1 mL
INACTIVE INGREDIENTS: EDETATE DISODIUM; SAFFLOWER OIL; COCONUT OIL; COCAMIDOPROPYL DIMETHYLAMINE; GLYCERIN; COCOA BUTTER; ALOE VERA LEAF; SHEA BUTTER; PEG-100 STEARATE; HEXYLENE GLYCOL; POLYSORBATE 60; ALMOND OIL; OLIVE OIL; PHENOXYETHANOL; POLYSORBATE 80; TOCOPHEROL; LEVOMENOL; CETOSTEARYL ALCOHOL; ISOHEXADECANE; CAPRYLYL GLYCOL; CITRIC ACID MONOHYDRATE; WATER; MEDIUM-CHAIN TRIGLYCERIDES; GLYCERYL MONOSTEARATE; HYDROXYETHYL ACRYLATE/SODIUM ACRYLOYLDIMETHYL TAURATE COPOLYMER (45000 MPA.S AT 1%); SORBITOL

WALGREENS DAILY REPAIR PSORIASIS MOISTURIZER

Active Ingredient

Salicylic Acid 3.0%

Purpose

Psoriasis Treatment

INDICATIONS AND USAGE

Uses Relieves and helps prevent recurrence of skin

- itching
- irritation
- redness
- flaking
- scaling associates with psoriasis.

Warnings

For external use only

Ask a doctor before use if you have

- psoriasis that covers a large area of the body.

When using this product

- avoid contact with eyes. If contact occurs, rinse eyes thoroughly with water.

Stop use and ask a doctor if

- condition worsens or does not improve after regular use of this product as directed.

Keep out of reach of children. If swallowed, get medical help or contact a Poison Control Center right away.

Directions

- Apply to affected areas one to four times daily or as directed by a doctor.

Other information

- may stain some fabrics

Inactive Ingredients

water, cocamidopropyl dimethylamine, butyrospermum parkii (shea) butter, glycerin, caprylic/capric triglyceride, theobroma cacao (cocoa) seed butter, cetearyl alcohol, cocos nucifera (coconut) oil, glyceryl stearate, PEG-100 stearate, hydroxyethyl acrylate/sodium acryloyldimethyl taurate copolymer, sorbitol, isohexadecane, prunus amygdalus dulcis (sweet almond) oil, carthamus tinctorius (safflower) seed oil, aloe barbadensis leaf juice, olea europaea (olive) fruit oil, phenoxyethanol, caprylyl glycol, hexylene glycol, polysorbate 60, polysorbate 80, tocopherol, bisabolol, citric acid, disodium EDTA.

Questions or comments? 1-800-925-4733

PACKAGE LABEL

WALGREENS DAILY REPAIR PSORIASIS MOISTURIZER

4 FL OZ. (118mL)

NDC 0363-0920-04